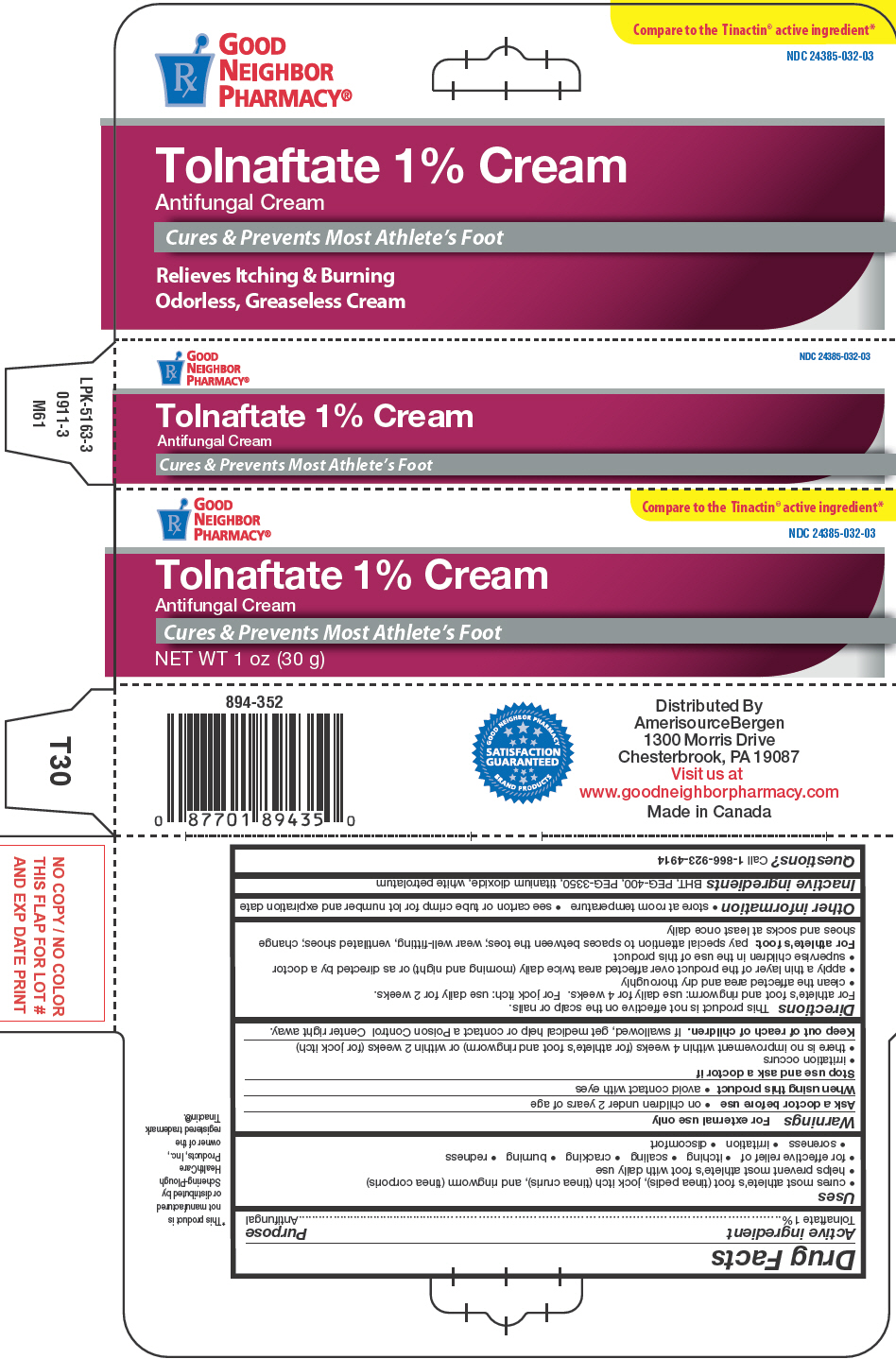 DRUG LABEL: Tolnaftate

NDC: 24385-032 | Form: CREAM
Manufacturer: Amerisource Bergen
Category: otc | Type: HUMAN OTC DRUG LABEL
Date: 20250715

ACTIVE INGREDIENTS: TOLNAFTATE 10 mg/1 g
INACTIVE INGREDIENTS: BUTYLATED HYDROXYTOLUENE; POLYETHYLENE GLYCOL 400; TITANIUM DIOXIDE; PETROLATUM

Tolnaftate 1% Cream
Antifungal Cream

Drug Facts

Active ingredient

Tolnaftate 1%

Purpose

Antifungal

Uses

- cures most athlete's foot (tinea pedis), jock itch (tinea cruris), and ringworm (tinea corporis)
- helps prevent most athlete's foot with daily use
- for effective relief of
  - itching
  - scaling
  - cracking
  - burning
  - redness
  - soreness
  - irritation
  - discomfort

Warnings

For external use only

Ask a doctor before use

- on children under 2 years of age

When using this product

- avoid contact with eyes

Stop use and ask a doctor if

- irritation occurs
- there is no improvement within 4 weeks (for athlete's foot and ringworm) or within 2 weeks (for jock itch)

Keep out of reach of children.If swallowed, get medical help or contact a Poison Control Center right away.

Directions

This product is not effective on the scalp or nails.

For athlete's foot and ringworm: use daily for 4 weeks. For jock itch: use daily for 2 weeks.

- clean the affected area and dry thoroughly
- apply a thin layer of the product over affected area twice daily (morning and night) or as directed by a doctor
- supervise children in the use of this product

For athlete's foot

pay special attention to spaces between the toes; wear well-fitting, ventilated shoes; change shoes and socks at least once daily

Other information

- store at room temperature
- see carton or tube crimp for lot number and expiration date

Inactive ingredients

BHT, PEG-400, PEG-3350, titanium dioxide, white petrolatum

Questions?

Call 1-866-923-4914

Distributed By
AmerisourceBergen
1300 Morris Drive
Chesterbrook, PA 19087

PRINCIPAL DISPLAY PANEL - 30 g Tube Carton

GOOD
NEIGHBOR
PHARMACY®

Compare to the Tinactin®active ingredient*

NDC 24385-032-03

Tolnaftate 1% Cream
Antifungal Cream

Cures & Prevents Most Athlete's Foot

NET WT 1 oz (30 g)